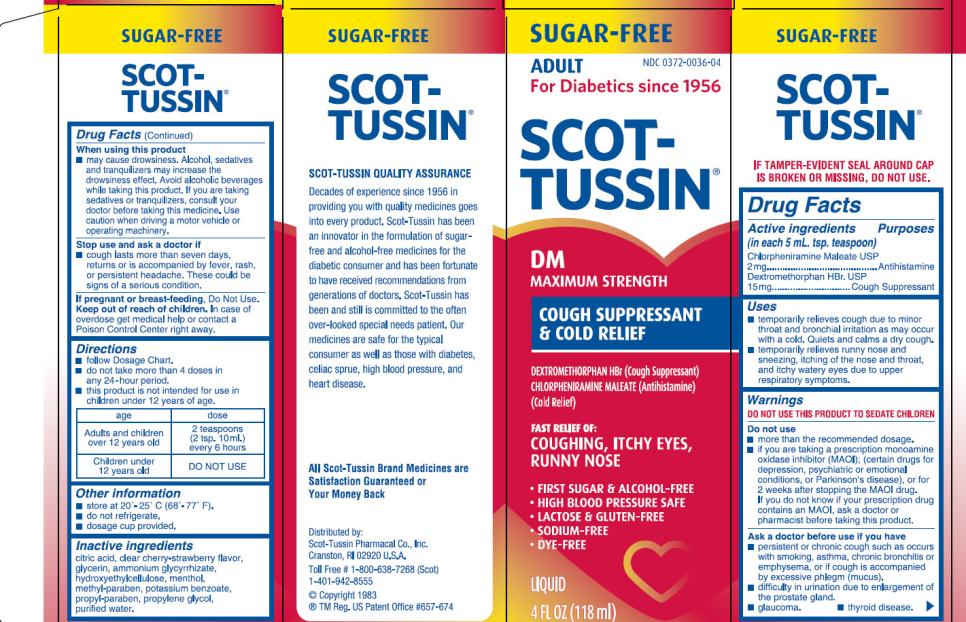 DRUG LABEL: Scot-Tussin
NDC: 0372-0036 | Form: LIQUID
Manufacturer: SCOT-TUSSIN Pharmacal Co., Inc.
Category: otc | Type: HUMAN OTC DRUG LABEL
Date: 20130129

ACTIVE INGREDIENTS: DEXTROMETHORPHAN HYDROBROMIDE 15 mg/5 mL; CHLORPHENIRAMINE MALEATE 2 mg/5 mL
INACTIVE INGREDIENTS: AMMONIUM GLYCYRRHIZATE; CITRIC ACID MONOHYDRATE; GLYCERIN; HYDROXYETHYL CELLULOSE (2000 MPA.S AT 1%); MENTHOL; METHYLPARABEN; POTASSIUM BENZOATE; PROPYLENE GLYCOL; PROPYLPARABEN; WATER

Scot-Tussin DM SF Maximum Strength Cough Cold

Active Ingredients

(in each 5 mL. tsp. teaspoon)

*Chlorpheniramine Maleate USP 2mg

Dextromethorphan HBr. USP 15mg

Purpose

Antihistamine

Cough Suppressant

Uses

- Temporarily relieves cough due to minor throat and bronchial irritation as may occur with a cold. Quiets and calms a dry cough.
- Temporarily relieves runny nose and sneezing, itching of the nose and throat, and itchy watery eyes due to upper respiratory symptoms.

Warnings

DO NOT USE THIS PRODUCT TO SEDATE CHILDREN

Do not use

- more than the recommended dosage.
- if you are taking a prescription monoamine oxidase inhibitor (MAOI); (certain drugs for depression, psychiatric, or emotional conditions, or Parkinson’s disease) or for 2 weeks after stopping the MAOI drug. If you do not know if your prescription drug contains an MAOI, ask a doctor or pharmacists before taking this product.

Ask a doctor before use is you have

- Persistent or a chronic cough such as occurs with smoking, asthma, chronic bronchitis or emphysema, or if cough is accompanied by excessive phlegm (mucus).
- Difficulty in urination due to enlargement of the prostate gland.
- Glaucoma.
- Thyroid disease.

When using this product

- May cause drowsiness. Alcohol, sedatives and tranquilizers may increase the drowsiness effect. Avoid alcoholic beverages while taking this product. If you are taking sedatives or tranquilizers, consult your doctor before taking this medicine. Use caution when driving a motor vehicle or operating machinery.

Stop use and ask a doctor if

- Chough lasts more than seven days, returns or is accompanied by fever, rash or persistent headache. These could be signs of a serious condition.

If pregnant or breast-feeding,

Do Not Use.

Keep out of reach of children.

In case of overdose get medical help or contact a Poison Control Center right away.

Directions:

- Follow Dosage Chart.
- Do not take more than 4 doses in any 24 hour period.
- This product is not intended for use in children under 12 years of age.

age | dose
Adults and children over 12 years old | 2 teaspoons (2 tsp. 10 ml) every 6 hours
Children Under 12 years old | DO NOT USE

Other Information

- Store at 20º – 25º C (68º – 77º F).
- Do not refrigerate.
- Dosage cup provided.

Inactive Ingredients

Ammonium Glycrrhizate, Citric Acid, Clear Cherry-Strawberry Flavor, Glycerin, Hydroxyethylcellulose, Menthol, Methyl Paraben, Potassium Benzoate, Propyl Paraben, Propylene Glycol, Purified Water.

PRINCIPAL DISPLAY PANEL

NDC 0372-0036-04

SCOT-TUSSIN

DM

Maximum Strength
COUGH SUPPRESSANT & COLD RELIEF

4 FL OZ (118 ml)